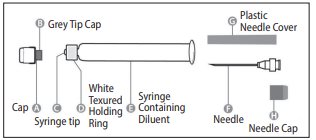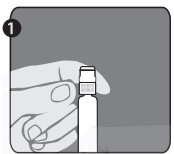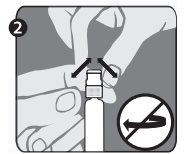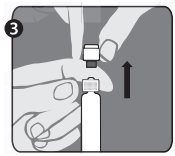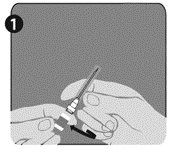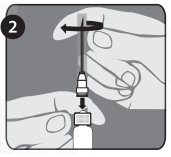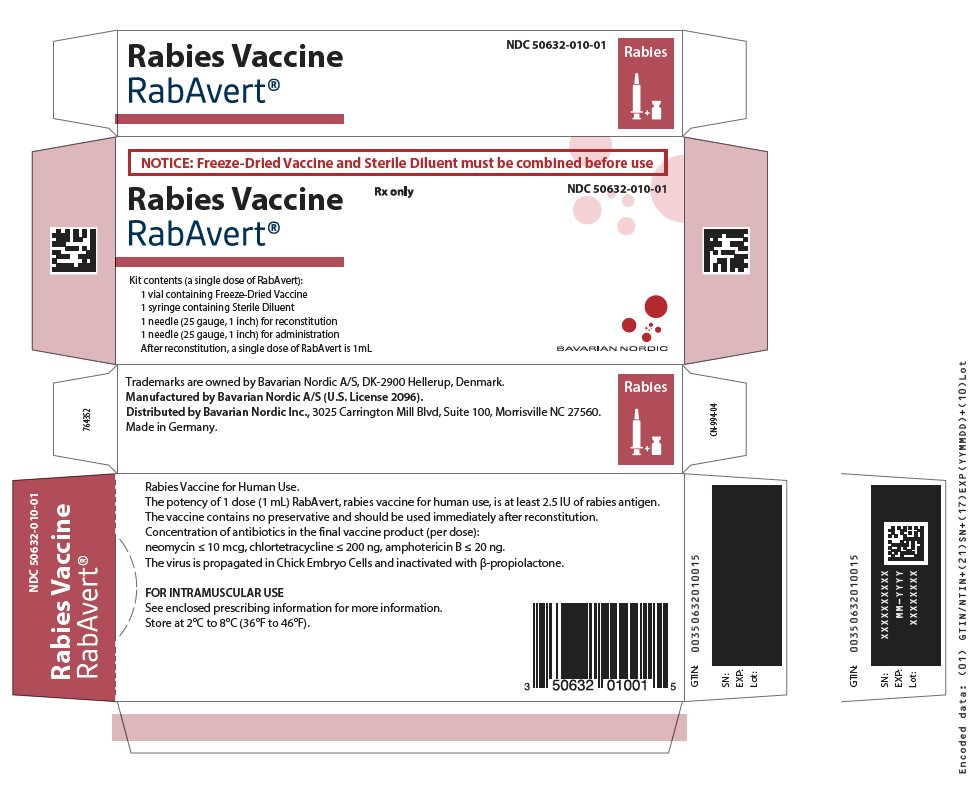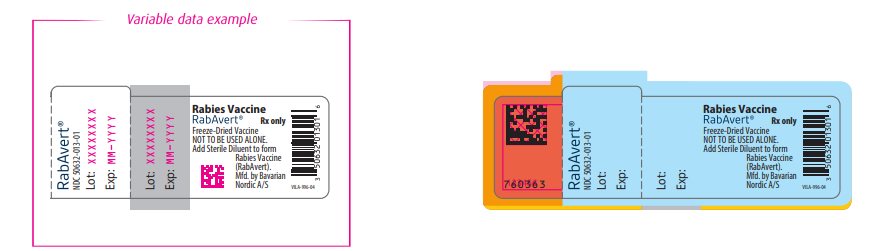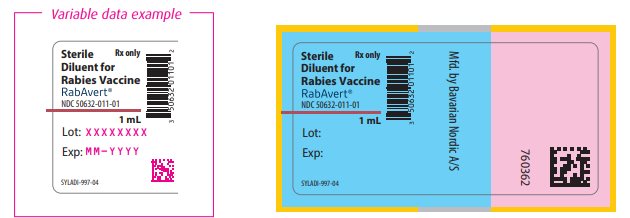 DRUG LABEL: RabAvert
NDC: 50632-010 | Form: KIT | Route: INTRAMUSCULAR
Manufacturer: Bavarian Nordic A/S
Category: other | Type: VACCINE LABEL
Date: 20250207

ACTIVE INGREDIENTS: RABIES VIRUS STRAIN FLURY LEP ANTIGEN (PROPIOLACTONE INACTIVATED) 2.5 [iU]/1 mL
INACTIVE INGREDIENTS: Tromethamine; Sodium chloride; EDETATE DISODIUM; POTASSIUM GLUCONATE; Water

PRESCRIBING INFORMATION
RabAvert®
Rabies Vaccine

Rabies Vaccine for Human Use

DESCRIPTION

RabAvert Rabies Vaccine is a sterile, freeze-dried vaccine obtained by growing the fixed-virus strain Flury Low Egg Passage (LEP) in primary cultures of chicken fibroblasts. The strain Flury LEP was obtained from American Type Culture Collection as the 59th egg passage. The growth medium for propagation of the virus is a synthetic cell culture medium with the addition of human albumin, polygeline (processed bovine gelatin), and antibiotics. The virus is inactivated with βpropiolactone and further processed by zonal centrifugation in a sucrose density gradient. The vaccine is lyophilized after addition of a stabilizer solution that consists of buffered polygeline and potassium glutamate. One dose of reconstituted vaccine contains ≤12 mg polygeline (processed bovine gelatin), ≤0.3 mg human serum albumin, 1 mg potassium glutamate, and 0.3 mg sodium EDTA. Small quantities of bovine serum are used in the cell culture process. Bovine components originate only from the United States, Australia, and New Zealand. Minimal amounts of chicken protein may be present in the final product; ovalbumin content is ≤3 ng/dose (1 mL), based on ELISA. Antibiotics (neomycin, chlortetracycline, amphotericin B) added during cell and virus propagation are largely removed during subsequent steps in the manufacturing process. In the final vaccine, neomycin is present at ≤10 mcg, chlortetracycline at ≤200 ng, and amphotericin B at ≤20 ng per dose. RabAvert is intended for intramuscular (IM) injection. The vaccine contains no preservative and should be used immediately after reconstitution with the supplied Sterile Diluent for RabAvert (Water for Injection). The potency of the final product is determined by the National Institutes of Health (NIH) mouse potency test using the United States (US) reference standard. The potency of 1 dose (1.0 mL) of RabAvert is at least 2.5 IU of rabies antigen. RabAvert is a white, freeze-dried vaccine for reconstitution with the diluent prior to use; the reconstituted vaccine is a clear to slightly opalescent, colorless to slightly pink suspension.

CLINICAL PHARMACOLOGY

Rabies in the United States: Over the last 100 years, the epidemiology of rabies in animals in the US has changed dramatically. More than 90% of all animal rabies cases reported annually to the Centers for Disease Control and Prevention (CDC) now occur in wildlife, whereas before 1960 the majority was in domestic animals. The principal rabies hosts today are wild terrestrial carnivores and bats. Annual human deaths have fallen from more than a hundred at the turn of the century to 1 to 2 per year despite major epizootics of animal rabies in several geographic areas. Within the US, only Hawaii has remained rabies free. Although rabies among humans is rare in the US, every year tens of thousands of people receive rabies vaccine for postexposure prophylaxis.

Rabies is a viral infection transmitted via the saliva of infected mammals. The virus enters the central nervous system of the host, causing an encephalomyelitis that is almost invariably fatal. The incubation period varies between 5 days and several years, but is usually between 20 and 60 days. Clinical rabies presents either in a furious or in a paralytic form. Clinical illness most often starts with prodromal complaints of malaise, anorexia, fatigue, headache, and fever followed by pain or paresthesia at the site of exposure. Anxiety, agitation, and irritability may be prominent during this period, followed by hyperactivity; disorientation; seizures; aerophobia and hydrophobia; hypersalivation; and eventually paralysis, coma, and death.

Modern day prophylaxis has proven nearly 100% successful; most human fatalities now occur in people who fail to seek medical treatment, usually because they do not recognize a risk in the animal contact leading to the infection. Inappropriate postexposure prophylaxis may also result in clinical rabies. Survival after clinical rabies is extremely rare, and is associated with severe brain damage and permanent disability.

RabAvert (in combination with passive immunization with Human Rabies Immune Globulin [HRIG] and local wound treatment) in postexposure treatment against rabies has been shown to protect patients of all age groups from rabies, when the vaccine was administered according to CDC’s Advisory Committee on Immunization Practices (ACIP) or World Health Organization (WHO) guidelines and as soon as possible after rabid animal contact. Anti-rabies antibody titers after immunization have been shown to reach levels well above the minimum antibody titer accepted as seroconversion (protective titer) within 14 days after initiating the postexposure treatment series. The minimum antibody titer accepted as seroconversion is a 1:5 titer (complete inhibition in the rapid fluorescent focus inhibition test [RFFIT] at 1:5 dilution) as specified by CDC^1 or ≥0.5 IU/mL as specified by WHO.^2,3

Clinical Studies:

Preexposure Vaccination: The immunogenicity of RabAvert was demonstrated in clinical trials conducted in different countries such as the US,^4,5 the United Kingdom (UK),^6 Croatia,^7 and Thailand.^8-10 When administered according to the recommended immunization schedule (Days 0, 7, and 21 or 0, 7, and 28), 100% of subjects attained a protective titer. In 2 studies carried out in the US in 101 subjects, antibody titers >0.5 IU/mL were obtained by Day 28 in all subjects. In studies carried out in Thailand in 22 subjects and in Croatia in 25 subjects, antibody titers of >0.5 IU/mL were obtained by Day 14 (injections on Days 0, 7, and 21) in all subjects.

The ability of RabAvert to boost previously immunized subjects was evaluated in 3 clinical trials. In the Thailand study, preexposure booster doses were administered to 10 individuals. Antibody titers of >0.5 IU/mL were present at baseline on Day 0 in all subjects.^9 Titers after a booster dose were enhanced from geometric mean titers (GMTs) of 1.91 to 23.66 IU/mL on Day 30. In an additional booster study, individuals known to have been immunized with Human Diploid Cell Vaccine (HDCV) were boosted with RabAvert. In this study, a booster response was observed on Day 14 for all individuals (22/22).^11 In a trial carried out in the US,^4 an IM booster dose of RabAvert resulted in a significant increase in titers in all subjects (35/35), regardless of whether they had received RabAvert or HDCV as the primary vaccine.

Persistence of antibody after immunization with RabAvert was evaluated. In a trial performed in the UK, neutralizing antibody titers >0.5 IU/mL were present 2 years after immunization in all sera (6/6) tested.

Preexposure Vaccination in Children: Preexposure administration of RabAvert in 11 Thai children aged 2 years and older resulted in antibody levels higher than 0.5 IU/mL on Day 14 in all children.^12

Postexposure Treatment: RabAvert, when used in the recommended postexposure WHO program of 5 to 6 IM injections of 1 mL (Days 0, 3, 7, 14, and 30 and optionally on Day 90) provided protective titers of neutralizing antibody (>0.5 IU/mL) in 158/160 patients^8,9,13-16 within 14 days and in 215/216 patients by Days 28 to 38.

Of these, 203 were followed for at least 10 months. No case of rabies was observed.^8,9,13-20 Some patients received HRIG, 20 to 30 IU/kg body weight, or Equine Rabies Immune Globulin (ERIG), 40 IU/kg body weight, at the time of the first dose. In most studies,^8,9,13,17 the addition of either HRIG or ERIG caused a slight decrease in GMTs which was neither clinically relevant nor statistically significant. In one study,^16 patients receiving HRIG had significantly lower (P<0.05) GMTs on Day 14; however, this was not clinically relevant. After Day 14 there was no statistical significance.

The results of several studies of normal volunteers receiving the postexposure WHO regimen, i.e., “simulated” postexposure, showed that with sampling by Days 28 to 30, 205/208 vaccinees had protective titers >0.5 IU/mL.

No postexposure vaccine failures have occurred in the US since cell culture vaccines have been routinely used.^1 Failures have occurred abroad, almost always after deviation from the recommended postexposure treatment protocol.^21-24 In 2 cases with bites to the face, treatment failed although no deviation from the recommended postexposure treatment protocol appeared to have occurred.^25

Postexposure Treatment in Children: In a 10-year serosurveillance study, RabAvert was administered to 91 children aged 1 to 5 years and 436 children and adolescents aged 6 to 20 years.^19 The vaccine was effective in both age groups. None of these patients developed rabies.

One newborn received RabAvert on an immunization schedule of Days 0, 3, 7, 14, and 30; the antibody concentration on Day 37 was 2.34 IU/mL. There were no clinically significant adverse events.^26

INDICATIONS AND USAGE

RabAvert is indicated for preexposure vaccination, in both primary series and booster dose, and for postexposure prophylaxis against rabies in all age groups.

Usually an immunization series is initiated and completed with 1 vaccine product. No clinical studies have been conducted that document a change in efficacy or the frequency of adverse reactions when the series is completed with a second vaccine product. However, for booster immunization, RabAvert was shown to elicit protective antibody level responses in persons tested who received a primary series with HDCV.^4,11

Preexposure Vaccination: See Table 1 and DOSAGE AND ADMINISTRATION.

Preexposure vaccination consists of 3 doses of RabAvert 1.0 mL given intramuscularly (deltoid region), 1 each on Days 0, 7, and 21 or 28^1 (see also Table 1 for criteria for preexposure vaccination).

Preexposure vaccination does not eliminate the need for additional therapy after a known rabies exposure (see DOSAGE AND ADMINISTRATION: Postexposure Prophylaxis of Previously Immunized Persons).

Preexposure vaccination should be offered to persons in high-risk groups, such as veterinarians, animal handlers, wildlife officers in areas where animal rabies is enzootic, certain laboratory workers, and persons spending time in foreign countries where rabies is endemic. Persons whose activities bring them into contact with potentially rabid dogs, cats, foxes, skunks, bats, or other species at risk of having rabies should also be considered for preexposure vaccination. International travelers might be candidates for preexposure vaccination if they are likely to come in contact with animals in areas where dog rabies is enzootic and immediate access to appropriate medical care, including biologics, might be limited.^27,28

Preexposure vaccination is given for several reasons. First, it may provide protection to persons with inapparent exposure to rabies. Second, it may protect persons whose postexposure therapy might be expected to be delayed. Finally, although it does not eliminate the need for prompt therapy after a rabies exposure, it simplifies therapy by eliminating the need for globulin and decreasing the number of doses of vaccine needed. This is of particular importance for persons at high risk of being exposed in countries where the available rabies-immunizing products may carry a higher risk of adverse reactions.

In some instances, booster doses of vaccine should be administered to maintain a serum titer corresponding to at least complete neutralization at a 1:5 serum dilution by the RFFIT (Table 1); each booster immunization consists of a single dose. See CLINICAL PHARMACOLOGY. Serum antibody determinations to decide upon the need for a booster dose is suggested by ACIP and is considered cost effective.

Table 1. Rabies Preexposure Prophylaxis Guide – United States, 1999a
Risk Category and Nature of Risk | Typical Populations | Preexposure Prophylaxis Recommendations
Continuous. Virus present continuously, often in high concentrations. Specific exposures likely to go unrecognized. Bite, non-bite, or aerosol exposure. | Rabies research lab workers,b rabies biologics production workers. | Primary course. Serologic testing every 6 months; booster vaccination if antibody titer is below acceptable level.b
Frequent. Exposure usually episodic, with source recognized, but exposure might be unrecognized. Bite, non-bite, or aerosol exposure. | Rabies diagnostic lab workers,b spelunkers, veterinarians and staff, and animal-control and wildlife workers in rabies enzootic areas. | Primary course. Serologic testing every 2 years; booster vaccination if antibody titer is below acceptable level.c
Infrequent (greater than population-at-large). Exposure nearly always episodic with source recognized. Bite or non-bite exposure. | Veterinarians and animal-control and wildlife workers in areas with low rabies rates. Veterinary students. Travelers visiting areas where rabies is enzootic and immediate access to appropriate medical care including biologics is limited. | Primary course. No serologic testing or booster vaccination.c
Rare (population-at-large). Exposures always episodic with source recognized. Bite or non-bite exposure. | US population-at-large, including persons in rabies-epizootic areas. | No vaccination necessary.
a Adapted from the Recommendations of the Advisory Committee on Immunization Practices: Human Rabies Prevention – United States, 1999.^1
b Judgment of relative risk and extra monitoring of vaccination status of laboratory workers is the responsibility of the laboratory supervisor.^29
c Minimum acceptable antibody level is complete virus neutralization at a 1:5 serum dilution by rapid fluorescent focus inhibition test. A booster dose should be administered if the titer falls below this level.

Postexposure Treatment: See Table 2 and DOSAGE AND ADMINISTRATION.

The following recommendations are only a guide. In applying them, take into account the animal species involved, the circumstances of the bite or other exposure, the immunization status of the animal, and presence of rabies in the region (as outlined below). Local or state public health officials should be consulted if questions arise about the need for rabies prophylaxis.^1

Table 2. Rabies Postexposure Prophylaxis Guide – United States, 1999a
Animal Type | Evaluation and Disposition of Animal | Postexposure Prophylaxis Recommendations
Dogs, cats, and ferrets | Healthy and available for 10 days’ observation | Should not begin prophylaxis unless animal develops clinical signs of rabiesb
 | Rabid or suspected rabid | Immediately vaccinate
 | Unknown (e.g., escaped) | Consult public health officials
Skunks, raccoons, bats, foxes, and most other carnivores | Regarded as rabid unless animal proven negative by laboratory testsc | Consider immediate vaccination
Livestock, small rodents, lagomorphs (rabbits and hares), large rodents (woodchucks and beavers), and other mammals | Consider individually | Consult public health officials. Bites of squirrels, hamsters, guinea pigs, gerbils, chipmunks, rats, mice, other small rodents, rabbits, and hares almost never require antirabies postexposure prophylaxis.
a Adapted from the Recommendations of the Advisory Committee on Immunization Practices: Human Rabies Prevention – United States, 1999.^1
b During the 10-day observation period, begin postexposure prophylaxis at the first sign of rabies in a dog, cat, or ferret that has bitten someone. If the animal exhibits clinical signs of rabies, it should be euthanized immediately and tested.
c The animal should be euthanized and tested as soon as possible. Holding for observation is not recommended. Discontinue vaccine if immunofluorescence test results of the animal are negative.

In the US, the following factors should be considered before antirabies treatment is initiated.

Species of Biting Animal: Wild terrestrial animals (especially skunks, raccoons, foxes, and coyotes) and bats are the animals most commonly infected with rabies and are the most important potential source of infection for both humans and domestic animals. Unless a wild animal is tested and shown not to be rabid, postexposure prophylaxis should be initiated upon bite or non-bite exposure to the animals (see definition in “Type of Exposure” below). If treatment has been initiated and subsequent testing in a qualified laboratory shows the exposing animal is not rabid, postexposure prophylaxis can be discontinued.^1

The likelihood of rabies in a domestic animal varies from region to region; hence, the need for postexposure prophylaxis also varies.^1

Small rodents (such as squirrels, hamsters, guinea pigs, gerbils, chipmunks, rats, and mice) and lagomorphs (including rabbits and hares) are almost never found to be infected with rabies and have not been known to transmit rabies to humans in the US. Bites from large rodents such as woodchucks (including groundhogs) and beavers should be considered as possible rabies exposures, especially in regions where rabies is enzootic in raccoons.^30 In all cases involving rodents, the state or local health department should be consulted before a decision is made to initiate antirabies postexposure prophylaxis.^1

Circumstances of Biting Incident: An UNPROVOKED attack is more likely than a provoked attack to indicate the animal is rabid. Bites inflicted on a person attempting to feed or handle an apparently healthy animal should generally be regarded as PROVOKED. A currently vaccinated dog, cat, or ferret is unlikely to become infected with rabies.^1

Type of Exposure: Rabies is transmitted by introducing the virus into open cuts or wounds in skin or via mucous membranes. The likelihood of rabies infection varies with the nature and extent of exposure. Two categories of exposure should be considered:

Bite: Any penetration of the skin by teeth. Bites to highly innervated areas such as the face and hands carry the highest risk, but the site of the bite should not influence the decision to begin treatment. Recent epidemiologic data suggest that even the very limited injury inflicted by a bat bite (compared with lesions caused by terrestrial carnivores) should prompt consideration of postexposure prophylaxis unless the bat is available for testing and is negative for evidence of rabies.^1

Non-bite: The contamination of open wounds, abrasions, mucous membranes, or theoretically, scratches with saliva or other potentially infectious material (such as neural tissue) from a rabid animal constitutes a non-bite exposure. In all instances of potential human exposures involving bats, and the bat is not available for testing, postexposure prophylaxis might be appropriate even if a bite, scratch, or mucous membrane exposure is not apparent when there is reasonable probability that such exposure might have occurred. Postexposure prophylaxis can be considered for persons who were in the same room as the bat and who might be unaware that a bite or direct contact had occurred (e.g., a sleeping person awakens to find a bat in the room or an adult witnesses a bat in the room with a previously unattended child, mentally disabled person, or intoxicated person) and rabies cannot be ruled out by testing the bat. Other contact by itself, such as petting a rabid animal and contact with blood, urine, or feces (e.g., guano) of a rabid animal, does not constitute an exposure and is not an indication for prophylaxis. Because the rabies virus is inactivated by desiccation and ultraviolet irradiation, in general, if the material containing the virus is dry, the virus can be considered noninfectious. Two cases of rabies have been attributed to probable aerosol exposures in laboratories, and 2 cases of rabies in Texas could possibly have been due to airborne exposures in caves containing millions of bats.^1

The only documented cases for rabies from human-to-human transmission occurred in 8 patients, including 2 in the US, who received corneas transplanted from persons who died of rabies undiagnosed at the time of death.^1 Stringent guidelines for acceptance of donor corneas have been implemented to reduce this risk.

Bite and non-bite exposure from humans with rabies theoretically could transmit rabies, but no laboratory-diagnosed cases occurring under such situations have been documented. Each potential exposure to human rabies should be carefully evaluated to minimize unnecessary rabies prophylaxis.^1

Postexposure Treatment Schedule: See also DOSAGE AND ADMINISTRATION.

The essential components of rabies postexposure prophylaxis are prompt local treatment of wounds and administration of both HRIG and vaccine. A complete course of postexposure treatment for previously unvaccinated adults and children consists of a total of 5 doses of vaccine, each 1.0 mL: one IM injection (deltoid) on each of Days 0, 3, 7, 14, and 28. For previously immunized adults and children, a total of 2 doses of vaccine, each 1.0 mL: one IM injection (deltoid) on each of Days 0 and 3. No HRIG should be administered to previously vaccinated persons as it may blunt their rapid memory response to rabies antigen.

Local Treatment of Wounds: Immediate and thorough washing of all bite wounds and scratches with soap and water is an important measure for preventing rabies. In animal studies, thorough local wound cleansing alone has been shown to reduce markedly the likelihood of rabies. Whenever possible, bite injuries should not be sutured to avoid further and/or deeper contamination. Tetanus prophylaxis and measures to control bacterial infection should be given as indicated.^1

Postexposure Prophylaxis of Rabies: The regimen for postexposure prophylaxis depends on whether or not the patient has been previously immunized against rabies (see below). For persons who have not previously been immunized against rabies, the schedule consists of an initial IM injection of HRIG exactly 20 IU/kg body weight in total. If anatomically feasible, the FULL DOSE of HRIG should be thoroughly infiltrated in the area around and into the wounds. Any remaining volume of HRIG should be injected intramuscularly at a site distant from rabies vaccine administration. HRIG should never be administered in the same syringe or in the same anatomical site as the rabies vaccine. HRIG is administered only once (for specific instructions for HRIG use, see the product package insert). The HRIG injection is followed by a series of 5 individual injections of RabAvert (1.0 mL each) given intramuscularly on Days 0, 3, 7, 14, and 28. Postexposure rabies prophylaxis should begin the same day exposure occurred or as soon after exposure as possible. The combined use of HRIG and RabAvert is recommended by the CDC for both bite and non-bite exposures, regardless of the interval between exposure and initiation of treatment.

In the event that HRIG is not readily available for the initiation of treatment, it can be given through the seventh day after administration of the first dose of vaccine. HRIG is not indicated beyond the seventh day because an antibody response to RabAvert is presumed to have begun by that time.^1

The sooner treatment is begun after exposure, the better. However, there have been instances in which the decision to begin treatment was made as late as 6 months or longer after exposure due to delay in recognition that an exposure had occurred. Postexposure antirabies treatment should always include administration of both passive antibody (HRIG) and immunization, with the exception of persons who have previously received complete immunization regimens (preexposure or postexposure) with a cell culture vaccine, or persons who have been immunized with other types of vaccines and have had documented rabies antibody titers. Persons who have previously received rabies immunization should receive 2 IM doses of RabAvert: one on Day 0 and another on Day 3. They should not be given HRIG as this may blunt their rapid memory response to rabies antigen.

Postexposure Prophylaxis Outside the United States: If postexposure treatment is begun outside the US with regimens or biologics that are not used in the US, it may be prudent to provide additional treatment when the patient reaches the US. State or local health departments should be contacted for specific advice in such cases.^1

CONTRAINDICATIONS

Preexposure Prophylaxis:

Hypersensitivity: History of anaphylaxis to the vaccine or any of the vaccine components constitutes a contraindication to preexposure vaccination with this vaccine.

Postexposure Prophylaxis: In view of the almost invariably fatal outcome of rabies, there is no contraindication to postexposure prophylaxis, including pregnancy.^1

WARNINGS

Patients considered to be at risk of a severe hypersensitivity reaction to the vaccine or any of the vaccine components should receive an alternative rabies vaccine if a suitable product is available.

Anaphylaxis, meningitis; neuroparalytic events such as encephalitis, transient paralysis; Guillain-Barré Syndrome; myelitis; retrobulbar neuritis; and multiple sclerosis have been reported to be temporally associated with the use of RabAvert. See PRECAUTIONS and ADVERSE REACTIONS. A patient’s risk of developing rabies must be carefully considered, however, before deciding to discontinue immunization.

For intramuscular use only. For adults, the deltoid area is the preferred site of immunization; for small children and infants, administration into the anterolateral zone of the thigh is preferred. The use of the gluteal region should be avoided, since administration in this area may result in lower neutralizing antibody titers.^1

Unintentional intravascular injection may result in systemic reactions, including shock.

Syncope (fainting) can occur in association with administration of injectable vaccines, including RabAvert. Syncope can be accompanied by transient neurological signs such as visual disturbance, paresthesia, and tonic-clonic limb movements. Procedures should be in place to avoid falling injury and to restore cerebral perfusion following syncope. See PRECAUTIONS and ADVERSE REACTIONS.

Development of active immunity after vaccination may be impaired in immunocompromised individuals. Please refer to PRECAUTIONS: Drug Interactions.

This product contains albumin, a derivative of human blood. It is present in RabAvert at concentrations of ≤0.3 mg/dose. Based on effective donor screening and product manufacturing processes, it carries an extremely remote risk for transmission of viral diseases. A theoretical risk for transmission of Creutzfeld-Jakob disease (CJD) also is considered extremely remote. No cases of transmission of viral diseases or CJD have ever been identified for albumin.

PRECAUTIONS

GENERAL PRECAUTIONS

General: The healthcare provider should question the patient, parent, or guardian about (1) the current health status of the vaccinee and (2) reactions to a previous dose of RabAvert or a similar product. Preexposure vaccination should be postponed in the case of sick and convalescent persons and those considered to be in the incubation stage of an infectious disease. A separate, sterile syringe and needle should be used for each patient. Needles must not be recapped and should be properly disposed of. As with any rabies vaccine, vaccination with RabAvert may not protect 100% of susceptible individuals.

Hypersensitivity: RabAvert contains residues of egg and chicken proteins, such as ovalbumin. In instances where individuals have developed clinical symptoms of anaphylaxis such as generalized urticaria, upper airway (lip, tongue, throat, laryngeal, or epiglottal) edema, laryngeal spasm or bronchospasm, hypotension, or shock, following exposure to egg or chicken protein, the vaccine should only be administered by personnel with the capability and facilities to manage anaphylaxis post vaccination.

Since reconstituted RabAvert contains processed bovine gelatin and trace amounts of neomycin, chlortetracycline, and amphotericin B, the possibility of allergic reactions in individuals hypersensitive to these substances should be considered when administering the vaccine.

Epinephrine injection (1:1,000) must be immediately available should anaphylactic or other allergic reactions occur.

When a person with a history of hypersensitivity must be given RabAvert, antihistamines may be given; epinephrine (1:1,000), volume replacement, corticosteroids, and oxygen should be readily available to counteract anaphylactic reactions.

DRUG INTERACTIONS

Drug Interactions: Radiation therapy, antimalarials, corticosteroids, other immunosuppressive agents, and immunosuppressive illnesses can interfere with the development of active immunity after vaccination and may diminish the protective efficacy of the vaccine. Preexposure vaccination should be administered to such persons with the awareness that the immune response may be inadequate. Immunosuppressive agents should not be administered during postexposure therapy unless essential for the treatment of other conditions. When rabies postexposure prophylaxis is administered to persons receiving corticosteroids or other immunosuppressive therapy, or who are immunosuppressed, it is important that a serum sample on Day 14 (the day of the fourth vaccination) be tested for rabies antibody to ensure that an acceptable antibody response has been induced.^1

HRIG must not be administered at more than the recommended dose, since active immunization to the vaccine may be impaired.

No data are available regarding the concurrent administration of RabAvert with other vaccines.

CARCINOGENESIS AND MUTAGENESIS AND IMPAIRMENT OF FERTILITY

Carcinogenesis, Mutagenesis, Impairment of Fertility: Long-term studies with RabAvert have not been conducted to assess the potential for carcinogenesis, mutagenesis, or impairment of fertility.

PREGNANCY

Use in Pregnancy: Animal reproductive studies have not been conducted with RabAvert. It is also not known whether RabAvert can cause fetal harm when administered to a pregnant woman or can affect reproduction capacity. RabAvert should be given to a pregnant woman only if clearly needed. The ACIP has issued recommendations for use of rabies vaccine in pregnant women.^1

NURSING MOTHERS

Use in Nursing Mothers: It is not known whether RabAvert is excreted in animal or human milk, but many drugs are excreted in human milk. Although there are no data, because of the potential consequences of inadequately treated rabies exposure, nursing is not considered a contraindication to postexposure prophylaxis. If the risk of exposure to rabies is substantial, preexposure vaccination might also be indicated during nursing.

PEDIATRIC USE

Pediatric Use: Children and infants receive the same dose of 1 mL, given intramuscularly, as do adults.

Only limited data on the safety and efficacy of RabAvert in the pediatric age group are available. However, in 3 studies some preexposure and postexposure experience has been gained^12,19,26 (see CLINICAL PHARMACOLOGY: Clinical Studies).

GERIATRIC USE

Geriatric Use: Clinical studies of RabAvert did not include sufficient numbers of subjects aged 65 and older to determine whether they respond differently from younger subjects. Other reported clinical experience has not identified differences in responses between the elderly and younger patients.

ADVERSE REACTIONS

In very rare cases, neurological and neuroparalytical events have been reported in temporal association with administration of RabAvert (see WARNINGS). These include cases of hypersensitivity (see CONTRAINDICATIONS, WARNINGS, and PRECAUTIONS).

The most commonly occurring adverse reactions are injection site reactions, such as injection site erythema, induration, and pain; flu-like symptoms, such as asthenia, fatigue, fever, headache, myalgia, and malaise; arthralgia; dizziness; lymphadenopathy; nausea; and rash.

A patient’s risk of acquiring rabies must be carefully considered before deciding to discontinue vaccination. Advice and assistance on the management of serious adverse reactions for persons receiving rabies vaccines may be sought from the state health department or CDC (see CONTRAINDICATIONS).

Local reactions such as induration, swelling, and reddening have been reported more often than systemic reactions. In a comparative trial in normal volunteers, Dreesen et al..^4 described their experience with RabAvert compared with an HDCV rabies vaccine. Nineteen subjects received RabAvert and 20 received HDCV. The most commonly reported adverse reaction was pain at the injection site, reported in 45% of the HDCV group and 34% of the group receiving RabAvert. Localized lymphadenopathy was reported in about 15% of each group. The most common systemic reactions were malaise (15% RabAvert vs. 25% HDCV), headache (10% RabAvert vs. 20% HDCV), and dizziness (15% RabAvert vs. 10% HDCV). In a recent study in the US^5, 83 subjects received RabAvert and 82 received HDCV. Again, the most common adverse reaction was pain at the injection site in 80% in the HDCV group and 84% in the group receiving RabAvert. The most common systemic reactions were headache (52% RabAvert vs. 45% HDCV), myalgia (53% RabAvert vs. 38% HDCV), and malaise (20% RabAvert vs. 17% HDCV). None of the adverse events were serious; almost all adverse events were of mild or moderate intensity. Statistically significant differences between vaccination groups were not found. Both vaccines were generally well tolerated.

Uncommonly observed adverse events include temperatures above 38°C (100°F), swollen lymph nodes, pain in limbs, and gastrointestinal complaints. In rare cases, patients have experienced severe headache, fatigue, circulatory reactions, sweating, chills, monoarthritis, and allergic reactions; transient paresthesias and 1 case of suspected urticaria pigmentosa have also been reported.

Observed During Clinical Practice (See WARNINGS and PRECAUTIONS): The following adverse reactions have been identified during post approval use of RabAvert. Because these reactions are reported voluntarily from a population of uncertain size, estimates of frequency cannot be made. These events have been chosen for inclusion due to their seriousness, frequency of reporting, causal connection to RabAvert, or a combination of these factors:

Allergic: Anaphylaxis, Type III hypersensitivity-like reactions, bronchospasm, urticaria, pruritus, edema.

Central Nervous System: Neuroparalysis, encephalitis, meningitis, transient paralysis, Guillain-Barré Syndrome, myelitis, retrobulbar neuritis, multiple sclerosis, presyncope, syncope, vertigo, visual disturbance.

Cardiac: Palpitations, hot flush.

Local: Extensive limb swelling.

Skin and Subcutaneous Tissue Disorders: Angioedema.

The use of corticosteroids to treat life-threatening neuroparalytic reactions may inhibit the development of immunity to rabies (see PRECAUTIONS, Drug Interactions).

Once initiated, rabies prophylaxis should not be interrupted or discontinued because of local or mild systemic adverse reactions to rabies vaccine. Usually such reactions can be successfully managed with anti-inflammatory and antipyretic agents.

Reporting of Adverse Events: Adverse events should be reported by the healthcare provider or patient to the US Department of Health and Human Services (DHHS) Vaccine Adverse Event Reporting System (VAERS). Report forms and information about reporting requirements or completion of the form can be obtained from VAERS by calling the toll-free number 1-800-822-7967.^1 In the US, such events can be reported to Bavarian Nordic: phone: 1-833-365-9596.

DOSAGE AND ADMINISTRATION

For intramuscular use only. The individual dose for adults, children, and infants is 1 mL.

In adults, administer vaccine by IM injection into the deltoid muscle. In small children and infants, administer vaccine into the anterolateral zone of the thigh. The gluteal area should be avoided for vaccine injections, since administration in this area may result in lower neutralizing antibody titers. Care should be taken to avoid injection into or near blood vessels and nerves. After aspiration, if blood or any suspicious discoloration appears in the syringe, do not inject but discard contents and repeat procedure using a new dose of vaccine at a different site.

Preexposure Dosage:

Primary Immunization: In the US, ACIP recommends 3 injections of 1 mL each: 1 injection on Day 0 and 1 on Day 7, and 1 either on Day 21 or 28 (for criteria for preexposure vaccination, see Table 1).

Booster Immunization: The individual booster dose is 1 mL, given intramuscularly.

Booster immunization is given to persons who have received previous rabies immunization and remain at increased risk of rabies exposure by reasons of occupation or avocation.

Persons who work with live rabies virus in research laboratories or vaccine production facilities (for continuous-risk category, see Table 1) should have a serum sample tested for rabies antibodies every 6 months. The minimum acceptable antibody level is complete virus neutralization at a 1:5 serum dilution by RFFIT. A booster dose should be administered if the titer falls below this level.

The frequent-risk category includes other laboratory workers such as those doing rabies diagnostic testing, spelunkers, veterinarians and staff, and animal-control and wildlife officers in areas where rabies is epizootic. Persons in the frequent-risk category should have a serum sample tested for rabies antibodies every 2 years and if the titer is less than complete neutralization at a 1:5 serum dilution by RFFIT should have a booster dose of vaccine. Alternatively, a booster can be administered in the absence of a titer determination.

The infrequent-risk category, including veterinarians, animal-control and wildlife officers working in areas of low rabies enzooticity (infrequent-exposure group), and international travelers to rabies enzootic areas, do not require routine preexposure booster doses of RabAvert after completion of a full primary preexposure vaccination scheme (Table 1).

Postexposure Dosage: Immunization should begin as soon as possible after exposure. A complete course of immunization consists of a total of 5 injections of 1 mL each: 1 injection on each of Days 0, 3, 7, 14, and 28 in conjunction with the administration of HRIG on Day 0. For children, see PRECAUTIONS: Pediatric Use.

Begin with the administration of HRIG. Give 20 IU/kg body weight.

This formula is applicable to all age groups, including infants and children. The recommended dosage of HRIG should not exceed 20 IU/kg body weight because it may otherwise interfere with active antibody production. Since vaccine-induced antibody appears within 1 week, HRIG is not indicated more than 7 days after initiating postexposure prophylaxis with RabAvert. If anatomically feasible, the FULL DOSE of HRIG should be thoroughly infiltrated in the area around and into the wounds. Any remaining volume of HRIG should be injected intramuscularly at a site distant from rabies vaccine administration. HRIG should never be administered in the same syringe or in the same anatomical site as the rabies vaccine.

Because the antibody response following the recommended immunization regimen with RabAvert has been satisfactory, routine post-immunization serologic testing is not recommended. Serologic testing is indicated in unusual circumstances, as when the patient is known to be immunosuppressed. Contact the appropriate state health department or CDC for recommendations.

Postexposure Prophylaxis of Previously Immunized Persons: When rabies exposure occurs in a previously vaccinated person, that person should receive 2 IM (deltoid) doses (1 mL each) of RabAvert: one immediately and one 3 days later. HRIG should not be given in these cases. Persons considered to have been immunized previously are those who received a complete preexposure vaccination or postexposure prophylaxis with RabAvert or other tissue culture vaccines or have been documented to have had a protective antibody response to another rabies vaccine. If the immune status of a previously vaccinated person is not known, full postexposure antirabies treatment (HRIG plus 5 doses of vaccine) is recommended. In such cases, if a protective titer can be demonstrated in a serum sample collected before vaccine is given, treatment can be discontinued after at least 2 doses of vaccine.

Instructions for Reconstituting RabAvert: RabAvert is supplied in a package that contains a vial of freeze-dried vaccine, a syringe containing 1 mL of sterile diluent, and two identical sterile needles: one needle is used to reconstitute the vaccine and the other needle is used to administer the vaccine intramuscularly following reconstitution.

Figures 1, 2, and 3 below present the syringe components, instructions for preparing the syringe, and attaching the needles to the syringe.

Figure 1: Sterile Diluent Pre-filled Syringe Components

Figure 2: Preparation of Syringe for Needle Attachment

Step 1: With one hand, hold the syringe containing diluent (E) with the cap pointing upward. Be sure to hold the syringe by the white textured holding ring (D).

Step 2: With the other hand, grasp the cap (A) and firmly rock it back and forth to break its connection to the white textured holding ring (D). Do not twist or turn the cap.

Step 3: Lift up to remove the cap (A) and the attached gray tip cap (B). Be careful not to touch the sterile syringe tip (C).

Figure 3: Attaching Needle to the Syringe

These instructions apply to both the needle used for reconstitution of the vaccine and the needle used for IM administration. Do not use the same needle for vaccine reconstitution and vaccine administration.

Step 1: Twist to remove the cap from one of the two identical needles. Do not remove the plastic cover (G).

Step 2: With one hand, firmly hold syringe (E) by white textured holding ring (D). With your other hand, insert this needle (F) and twist clockwise until it locks into place. Once the needle is locked, and the plastic cover (G) removed, it is ready for use.

Reconstitute the vaccine with the Sterile Diluent by inserting the needle at a 45° angle into the vial containing freeze-dried vaccine and slowly inject the entire contents of the diluent (1 mL). Mix gently to avoid foaming. The white, freeze-dried vaccine dissolves to give a clear to slightly opalescent, colorless to slightly pink suspension. Withdraw the total amount of dissolved vaccine into the syringe by inverting the vial and pulling the needle back close to the stopper. This will allow the full amount of vaccine solution to be withdrawn from the vial. Using the same method as described in Figure 3, replace the needle used for reconstitution with the second needle for vaccine administration.

Parenteral drug products should be inspected visually for particulate matter and discoloration prior to administration, whenever solution and container permit. If either of these conditions exists, the vaccine should not be administered. The reconstituted vaccine should be used immediately.

The lyophilization of the vaccine is performed under reduced pressure and the subsequent closure of the vials is done under vacuum. If there is no negative pressure in the vial, injection of Sterile Diluent for RabAvert would lead to an excess positive pressure in the vial. After reconstitution of the vaccine, it is recommended to unscrew the syringe from the needle to eliminate the negative pressure. After that, the vaccine can be easily withdrawn from the vial. It is not recommended to induce excess pressure, since over-pressurization may prevent withdrawing the proper amount of the vaccine.

HOW SUPPLIED

RabAvert product presentation is listed in Table 3.

Table 3. RabAvert Product Presentation
Presentation | Carton NDC Number | Components
Single-dose kit | 50632-010-01 | - 1 vial of Freeze-Dried Vaccine containing a single dose [NDC 50632-013-01] - 1 disposable prefilled syringe of Sterile Diluent for reconstitution (1 mL) [NDC 50632-011-01] - 1 needle for vaccine reconstitution (25 gauge, 1 inch) - 1 needle for vaccine administration (25 gauge, 1 inch)

RabAvert should be stored protected from light at 2°C to 8°C (36°F to 46°F). After reconstitution, the vaccine is to be used immediately. The vaccine may not be used after the expiration date given on package and container.

REFERENCES

1. CDC. Recommendations of the Advisory Committee on Immunization Practices (ACIP). Human Rabies Prevention – United States, 1999. Morbidity and Mortality Weekly Report Recommendations and Report, January 8, 1999, Vol.48, RR-1; 1.1-21.

2. Smith JS, Yager, PA & Baer, GM. A rapid reproducible test for determining rabies neutralizing antibody. Bull WHO. 1973; 48: 535-541.

3. Eighth Report of the WHO Expert Committee on Rabies. WHO Technical Report Series, no. 824; 1992.

4. Dreesen DW, et al. Two-year comparative trial on the immunogenicity and adverse effects of purified chick embryo cell rabies vaccine for preexposure immunization. Vaccine. 1989; 7: 397-400.

5. Dreesen, DW. Investigation of antibody response to purified chick embryo cell tissue culture vaccine (PCECV) or human diploid cell culture vaccine (HDCV) in healthy volunteers. Study synopsis 7USA401RA, September 1996 – December 1996 (unpublished).

6. Nicholson KG, et al. Preexposure studies with purified chick embryo cell culture rabies vaccine and human diploid cell vaccine: serological and clinical responses in man. Vaccine. 1987; 5: 208-210.

7. Vodopija I, et al. An evaluation of second generation tissue culture rabies vaccines for use in man: a four-vaccine comparative immunogenicity study using a preexposure vaccination schedule and an abbreviated 2-1-1 postexposure schedule. Vaccine. 1986; 4: 245-248.

8. Wasi C, et al. Purified chick embryo cell rabies vaccine (letter). Lancet. 1986; 1: 40.

9. Wasi C. Rabies prophylaxis with purified chick embryo (PCEC) rabies vaccine. Protocol 8T-201RA, 1983 - 1984 (unpublished).

10. Wasi C. Personal communication to Behringwerke AG, 1990.

11. Bijok U, et al. Clinical trials in healthy volunteers with the new purified chick embryo cell rabies vaccine for man. J Commun Dis. 1984; 16: 61-69.

12. Lumbiganon P, et al. Preexposure vaccination with purified chick embryo cell rabies vaccines in children. Asian Pacific J Allergy Immunol. 1989; 7: 99-101.

13 Vodopija I. Post-exposure rabies prophylaxis with purified chick embryo cell (PCEC) rabies vaccine. Protocol 7YU-201RA, 1983-1985 (unpublished).

14. John J. Evaluation of purified chick embryo cell culture (PCEC) rabies vaccine, 1987 (unpublished).

15. Tanphaichitra D, Siristonpun Y. Study of the efficacy of a purified chick embryo cell vaccine in patients bitten by rabid animals. Intern Med. 1987; 3: 158-160.

16. Thongcharoen P, et al. Effectiveness of new economical schedule of rabies postexposure prophylaxis using purified chick embryo cell tissue culture rabies vaccine. Protocol 7T301IP, 1993 (unpublished).

17. Ljubicic M, et al. Efficacy of PCEC vaccines in post-exposure rabies prophylaxis. In: Vodopija, Nicholson, Smerdel & Bijok (eds.): Improvements in rabies post-exposure treatment (Proceedings of a meeting in Dubrovnik, Yogoslavia). Zagreb Institute of Public Health 1985.17.

18. Madhusudana SN, Tripathi KK. Post exposure studies with human diploid cell rabies vaccine and purified chick embryo cell vaccine: Comparative Serological Responses in Man. Zbl Bakt 1989; 271: 345-350.

19. Sehgal S, et al. Ten year longitudinal study of efficacy and safety of purified chick embryo cell vaccine for pre- and postexposure prophylaxis of rabies in Indian population. J Commun Dis. 1995; 27: 36-43.

20. Sehgal S, et al. Clinical evaluation of purified chick embryo cell antirabies vaccine for postexposure treatment. J Commun Dis. 1988; 20: 293-300.

21. Fishbein DB, et al. Administration of human diploid-cell rabies vaccine in the gluteal area. N Engl J Med. 1988; 318: 124-125.

22. Shill M, et al. Fatal rabies encephalitis despite appropriate postexposure prophylaxis. A case report. N Engl J Med. 1987; 316: 1257-1258.

23. Wilde H, et al. Failure of rabies postexposure treatment in Thailand. Vaccine. 1989; 7: 49-52.

24. Kuwert EK, et al. postexposure use of human diploid cell culture rabies vaccine. Dev Biol Stand. 1977; 37: 273-286.

25. Hemachudha T, et al. Additional reports of failure to respond to treatment after rabies exposure in Thailand. Clin Infect Dis. 1999; 28: 143-144.

26. Lumbiganon P, Wasi C. Survival after rabies immunisation in newborn infant of affected mother. Lancet. 1990; 336: 319-320.

27. Centers for Disease Control and Prevention. Health Information for International Travel, 2003-2004 (The Yellow Book). Atlanta: US Department of Health and Human Services, Public Health Service, 2003. Internet version at: http://www.cdc.gov/travel/yb

28. World Health Organization. International Travel and Health, 2002. Geneva, Switzerland. Internet version at: http://www.who.int/ith

29. CDC and NIH. Biosafety in microbiological and biomedical laboratories. 3rd. ed. Washington, D.C. HHS Publication no. (CDC) 93-8395, Washington, DC: US Department of Health and Human Services, 1993.

30. Krebs JW, et al. Rabies surveillance in the United States in 2001. J Am Vet Med Assoc. 2002; 221: 1690-1701.

RabAvert is a trademark owned by Bavarian Nordic A/S.

Manufactured by:
Bavarian Nordic A/S, DK-2900 Hellerup, Denmark
US License No. 2096

Distributed by:
Bavarian Nordic Inc.,
3025 Carrington Mill Boulevard, suite 100, NC 27560
©2019 Bavarian Nordic A/S.

RAB:9PI
Rev. 02/2025

Principal Display Panel - Carton Label

NOTICE: Freeze-Dried Vaccine and Sterile Diluent must be combined before use

Rabies Vaccine

RabAvert®

Rx only

NDC 50632-010-01

Kit contents (a single dose of RabAvert):

1 vial containing Freeze-Dried Vaccine
1 syringe containing Sterile Diluent
1 needle (25 gauge, 1 inch) for reconstitution
1 needle (25 gauge, 1 inch) for administration
After reconstitution, a single dose of RabAvert is 1 mL

BAVARIAN NORDIC

Principal Display Panel - Vial Label

Rabies Vaccine
RabAvert® Rx only

Freeze-Dried Vaccine
NOT TO BE USED ALONE.
Add Sterile Diluent to form
Rabies Vaccine
(RabAvert).
Mfd. by Bavarian
Nordic A/S

VILA-996-04

Lot:

Exp:

Principal Display Panel - Diluent Label

Sterile Rx only
Diluent for
Rabies Vaccine
RabAvert®

NDC 50632-011-01

1 mL

Lot:

Exp:

SYLADI-997-04

Mfd. by Bavarian Nordic A/S